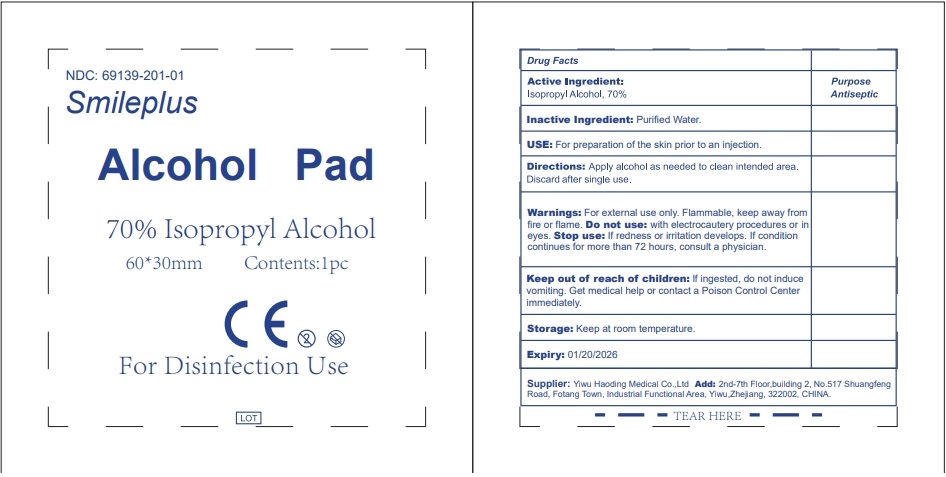 DRUG LABEL: Smileplus Alcohol Pad
NDC: 69139-201 | Form: SWAB
Manufacturer: YIWU HAODING MEDICAL CO.,LTD
Category: otc | Type: HUMAN OTC DRUG LABEL
Date: 20240109

ACTIVE INGREDIENTS: ALCOHOL 70 g/100 g
INACTIVE INGREDIENTS: WATER

DRUG FACTS

Active Ingredient

Isopropyl Alcohol 70%

Purpose

Antiseptic

Uses:

For preparation of the skin prior to an injection

Directions: Apply alcoho as needed to clean intended area. Discard after single use. Tear to open, keep at room temperature.

Discard after single use.

WARNINGS

For external use only.

Flammable, keep away from heat and flame.

Do not use: with electocautery procedures or in eyes

STOP USE

if redness or irritation develops. If condition continues for more than 72 hours, consult a physician.

Keep out of reach of children.

If ingested, do not induce vomiting. Get medical help or contact a Poison Control Center immediately.

Inactive Ingredients:

purified water